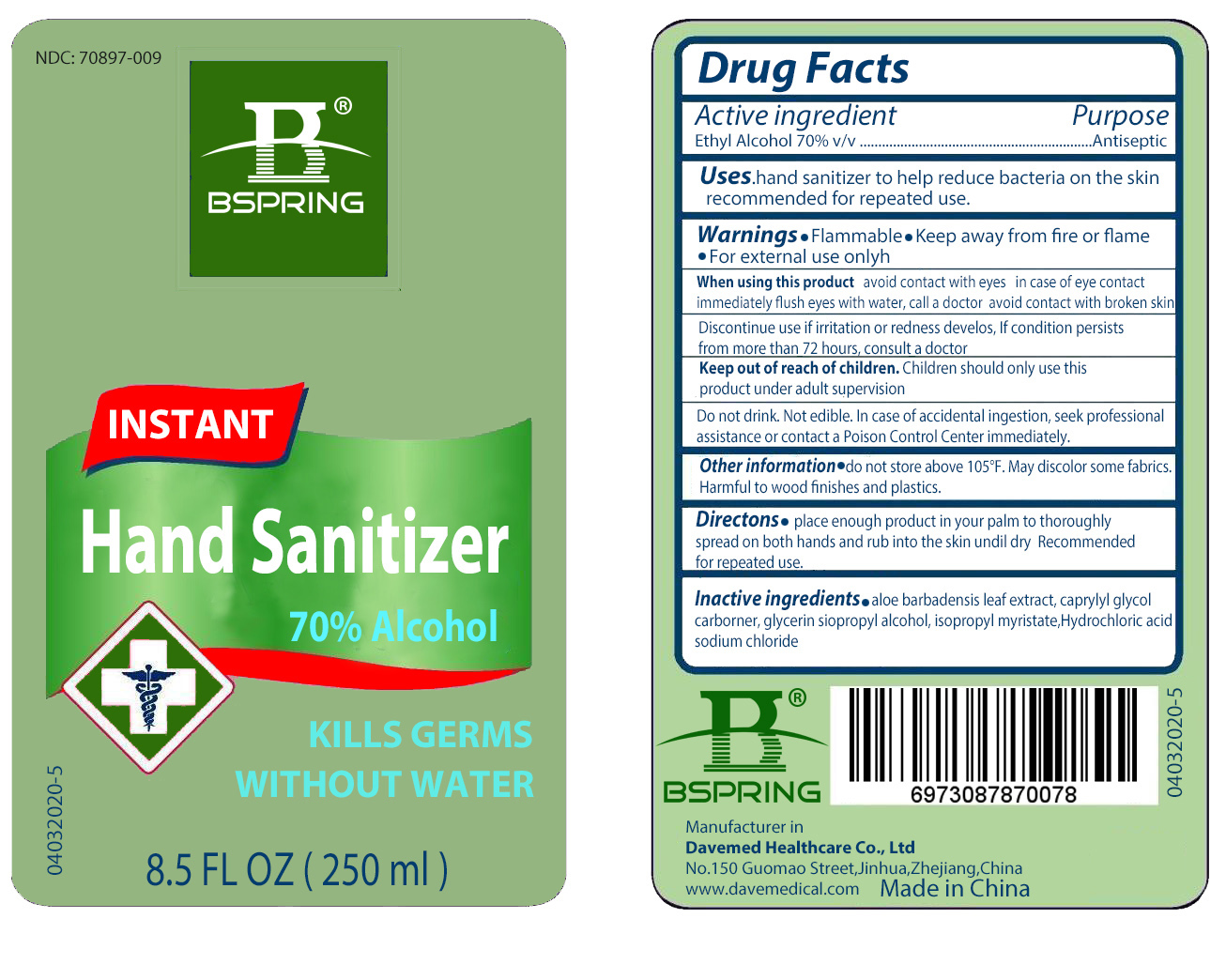 DRUG LABEL: Instant Hand Sanitizer
NDC: 70897-009 | Form: LIQUID
Manufacturer: Davemed Healthcare Co., Ltd
Category: otc | Type: HUMAN OTC DRUG LABEL
Date: 20200702

ACTIVE INGREDIENTS: ALCOHOL 70 mL/100 mL
INACTIVE INGREDIENTS: HYDROCHLORIC ACID; GLYCERIN; ISOPROPYL MYRISTATE; ISOPROPYL ALCOHOL; ALOE VERA LEAF; CARBOMER HOMOPOLYMER, UNSPECIFIED TYPE; CAPRYLYL GLYCOL; SODIUM CHLORIDE

Instant Hand Santizer

This is a hand sanitizer manufactured according to the Temporary Policy for Preparation of Certain Alcohol-Based Hand Sanitizer Products During the Public Health Emergency (CoViD-19); Guidance for Industry.

The hand sanitizer is manufactured using only the following United States Pharmacopoeia (USP) grade ingredients in the preparation of the product (percentage in final product formulation) consistent with World Health Organization (WHO) recommendations:

1. Alcohol (ethanol) (USP or Food Chemical Codex (FCC) grade) (80%, volume/volume (v/v)) in an aqueous solution denatured according to Alcohol and Tobacco Tax and Trade Bureau regulations in 27 CFR part 20.
2. Glycerol (1.45% v/v).
3. Hydrogen peroxide (0.125% v/v).
4. Sterile distilled water or boiled cold water.

The firm does not add other active or inactive ingredients. Different or additional ingredients may impact the quality and potency of the product.

Active Ingredient(s)

Alcohol 70% v/v. Purpose: Antiseptic

Purpose

Antiseptic, Hand Sanitizer

Use

Hand Sanitizer to help reduce bacteria on the skin. Recommended for repeated use

Warnings

Flammable.

Keep away from fire or flame

For external use only

When using this product

- avoid contact with eyes
- in case of eye contact, immediately flush eyes with water, call a doctor
- avoid contact with broken skin

Discontinue use if irrittion or redness develops. If condition persists for more than 72 hours, consult a doctor.

Keep out of reach of children. Children should only use this product under adult supervision

Do not drink. Not edible. In case of accidental ingestion, seek professional assistance or contact a Poison Control Center immediately.

Directions

- Place enough product in your palm to thoroughly spread on both hands and rub into the skin until dry. Recommended for repeated use

Other information

- Do not store above 105F
- May discolor some fabrics.
- Harmful to wood finishes and plastics

Inactive ingredients

aloe bardensis leaf extract, caprylyl glycol carbomer, glycerin, isopropyl alcohol, isopropyl myristate, hydrochloric acid, sodium chloride